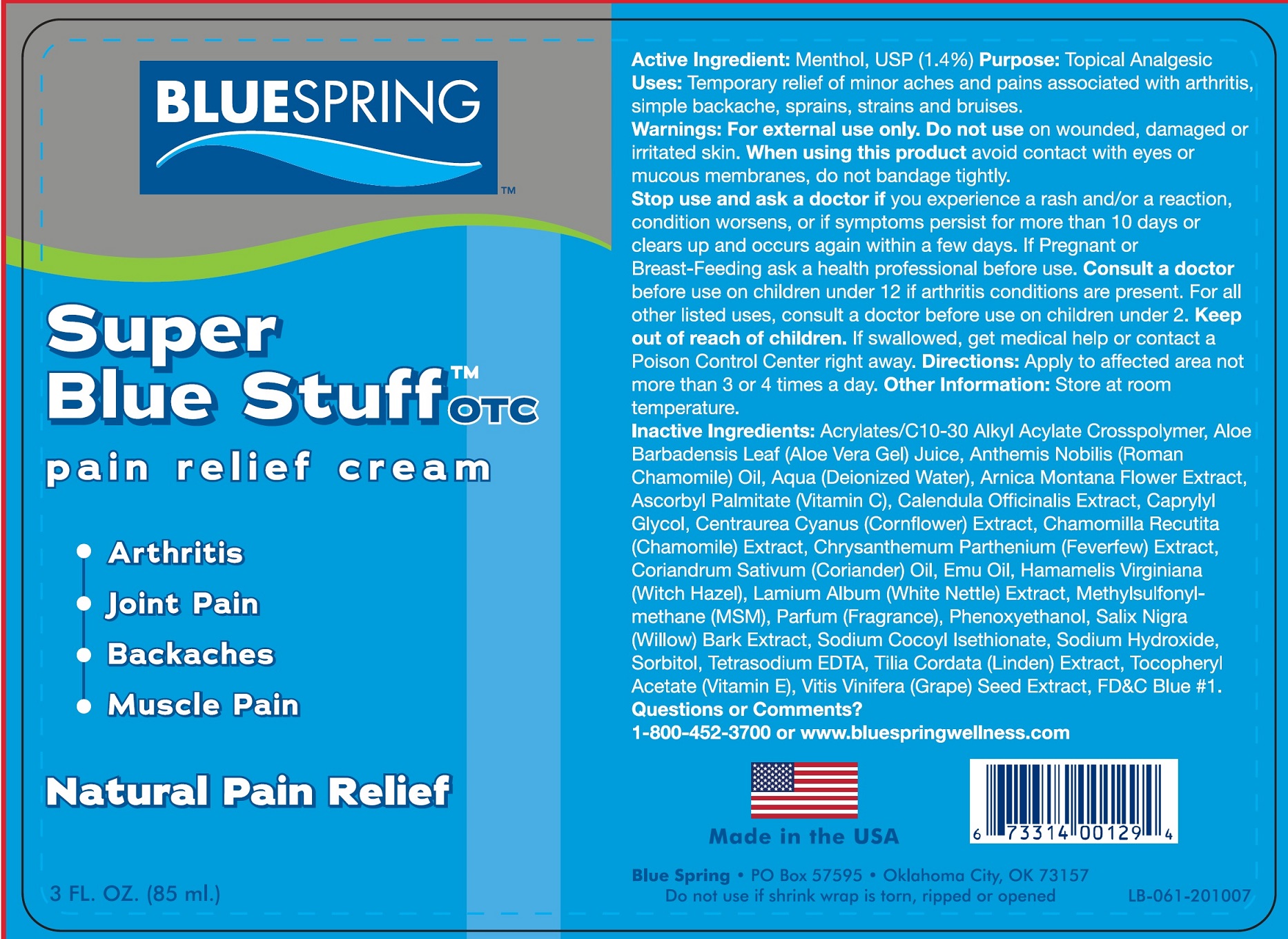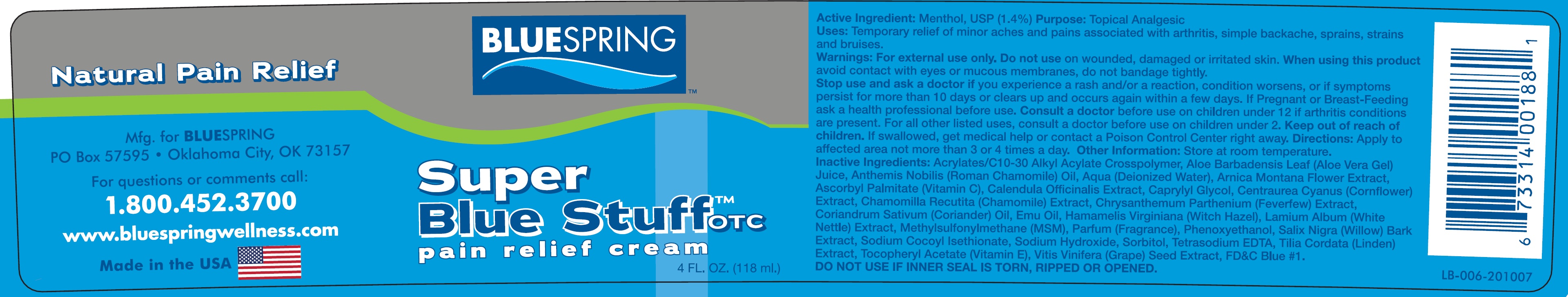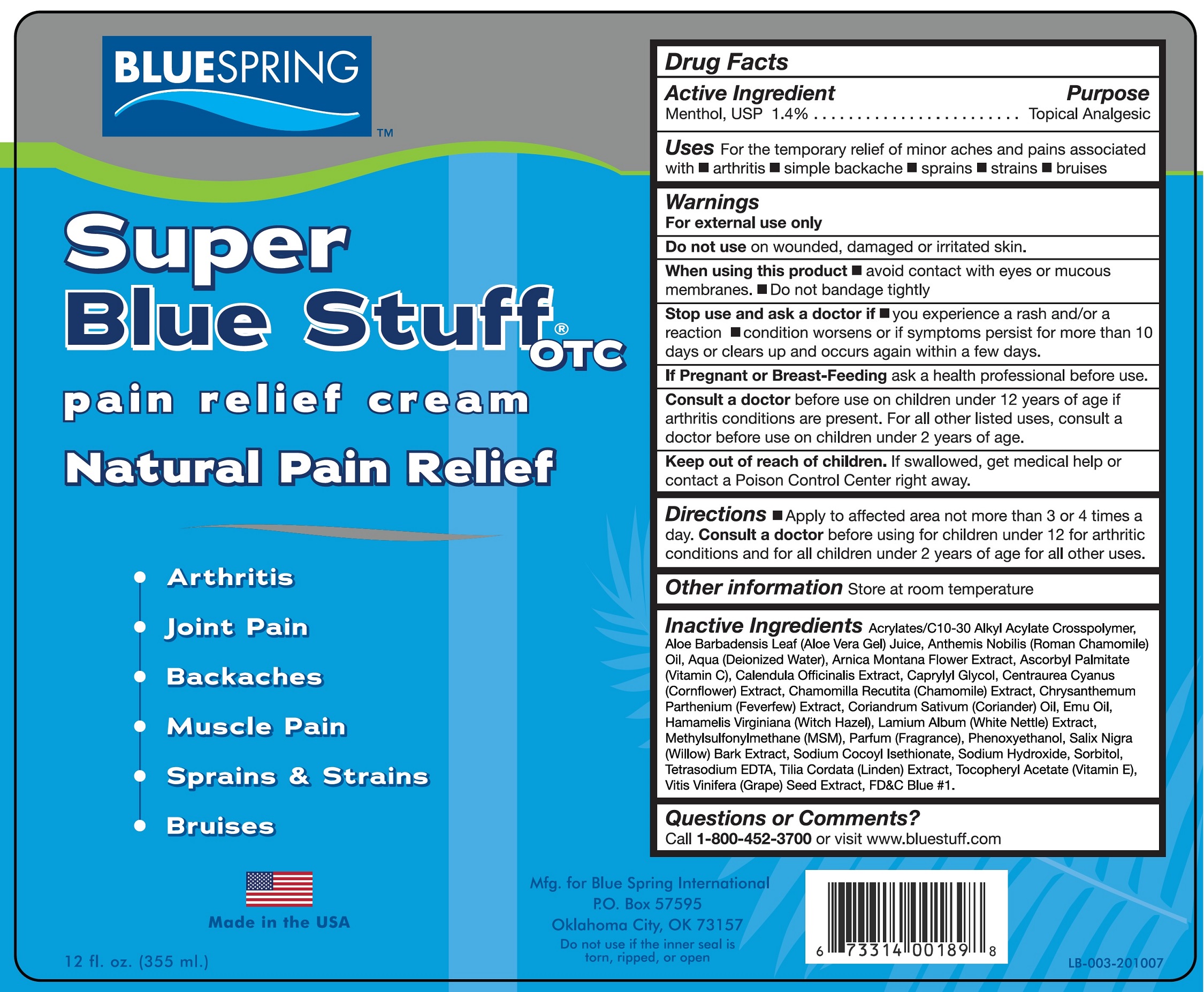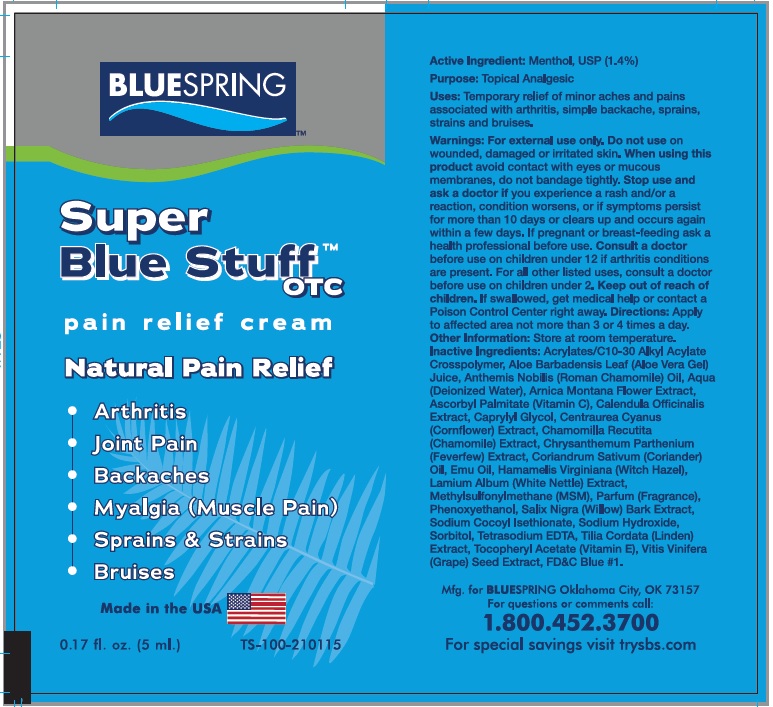 DRUG LABEL: SUPER BLUE STUFF Pain Relief Cream
NDC: 14448-314 | Form: CREAM
Manufacturer: BLUE SPRING WELLNESS, L.L.C.
Category: otc | Type: HUMAN OTC DRUG LABEL
Date: 20231110

ACTIVE INGREDIENTS: MENTHOL 14 mg/1 mL
INACTIVE INGREDIENTS: CARBOMER INTERPOLYMER TYPE A (ALLYL SUCROSE CROSSLINKED); ALOE VERA LEAF; CHAMAEMELUM NOBILE FLOWER OIL; WATER; ARNICA MONTANA FLOWER; ASCORBYL PALMITATE; CALENDULA OFFICINALIS FLOWER; CAPRYLYL GLYCOL; CENTAUREA CYANUS FLOWER; CORIANDER OIL; EMU OIL; HAMAMELIS VIRGINIANA TOP; LAMIUM ALBUM WHOLE; DIMETHYL SULFONE; PHENOXYETHANOL; SALIX NIGRA BARK; SODIUM COCOYL ISETHIONATE; SODIUM HYDROXIDE; SORBITOL; EDETATE SODIUM; TILIA CORDATA WHOLE; .ALPHA.-TOCOPHEROL ACETATE; VITIS VINIFERA SEED; FD&C BLUE NO. 1

SUPER BLUE STUFF Pain Relief Cream

Active Ingredient:

Menthol, USP (1.4%)

Purpose:

Topical Analgesic

Uses:

Temporary relief of minor aches and pains associated with arthritis, simple backache, sprains, strains and bruises.

Warnings:

For external use only.

Do not use

on wounded, damaged or irritated skin.

When using this product

avoid contact with eyes or mucous membranes, do not bandage tightly.

Stop use and ask a doctor if

you experience a rash and/or a reaction, condition worsens, or if symptoms persist for more than 10 days or clears up and occurs again within a few days.

If Pregnant or Breast-Feeding

ask a health professional before use.

Consult a doctor

before use on children under 12 if arthritis conditions are present. For all other listed uses, consult a doctor before use on children under 2.

Keep out of reach of children.

If swallowed, get medical help or contact a Poison Control Center right away.

Directions:

Apply to affected area not more than 3 or 4 time a day.

Other Information:

Store at room temperature.

Inactive Ingredients:

Acrylates/C10-30 Alkyl Acrylate Crosspolymer, Aloe Barbadensis Leaf(Aloe Vera Gel)Juice, Anthemis Nobilis (Roman Chamomile) Oil, Aqua (Deionized Water), Arnica Montana Flower Extract, Ascorbyl Palmitate (Vitamin C), Calendula Officinalis Extract, Caprylyl Glycol, Centraurea Cyanus (Cornflower) Extract, Coriandrum Sativum (Coriander) Oil, Emu Oil, Hamamelis Virginiana (Witch Hazel), Lamium Album (White Nettle) Extract, Methylsulfonylmethane (MSM), Parfum (Fragrance), Phenoxyethanol, Sali Nigra (Willow) Bark Extract, Sodium Cocoyl Isethionate, Sodium Hydroxide, Sorbitol, Tetrasodium EDTA, Tilia Cordata (Linden)Extract, Tocopheryl Acetate (Vitamin E), Vitis Vinifera (Grape) Seed Extract, FD&C Blue #1

Questions or Comments?

1-800-452-3700 or www.bluespringwellness.com